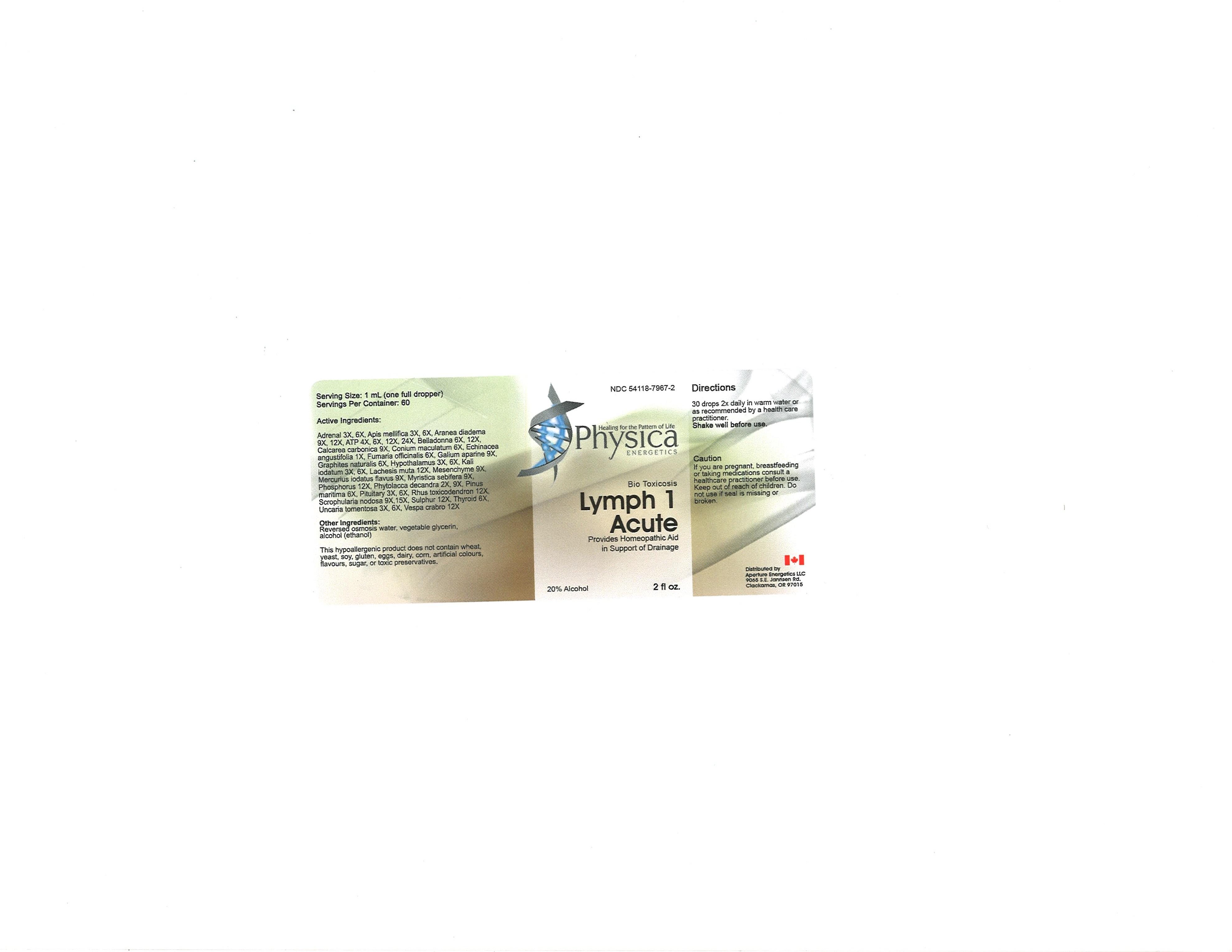 DRUG LABEL: Lymph 1 Acute
NDC: 54118-7967 | Form: SOLUTION/ DROPS
Manufacturer: ABCO Laboratories, Inc.
Category: homeopathic | Type: HUMAN OTC DRUG LABEL
Date: 20121010

ACTIVE INGREDIENTS: BOS TAURUS ADRENAL GLAND 3 [hp_X]/60 mL; APIS MELLIFERA 3 [hp_X]/60 mL; ARANEUS DIADEMATUS 9 [hp_X]/60 mL; ADENOSINE TRIPHOSPHATE 4 [hp_X]/60 mL; ATROPA BELLADONNA 6 [hp_X]/60 mL; OYSTER SHELL CALCIUM CARBONATE, CRUDE 9 [hp_X]/60 mL; CONIUM MACULATUM FLOWERING TOP 6 [hp_X]/60 mL; ECHINACEA ANGUSTIFOLIA 1 [hp_X]/60 mL; FUMARIA OFFICINALIS FLOWERING TOP 6 [hp_X]/60 mL; GALIUM APARINE 9 [hp_X]/60 mL; GRAPHITE 6 [hp_X]/60 mL; BOS TAURUS HYPOTHALAMUS 3 [hp_X]/60 mL; POTASSIUM IODIDE 3 [hp_X]/60 mL; LACHESIS MUTA VENOM 12 [hp_X]/60 mL; MERCUROUS IODIDE 9 [hp_X]/60 mL; VIROLA SEBIFERA RESIN 9 [hp_X]/60 mL; PHOSPHORUS 12 [hp_X]/60 mL; PHYTOLACCA AMERICANA ROOT 2 [hp_X]/60 mL; MARITIME PINE 6 [hp_X]/60 mL; BOS TAURUS PITUITARY GLAND 3 [hp_X]/60 mL; TOXICODENDRON PUBESCENS LEAF 12 [hp_X]/60 mL; SCROPHULARIA NODOSA 9 [hp_X]/60 mL; SULFUR 12 [hp_X]/60 mL; THYROID, BOVINE 6 [hp_X]/60 mL; UNCARIA TOMENTOSA LEAF 3 [hp_X]/60 mL; VESPA CRABRO 12 [hp_X]/60 mL
INACTIVE INGREDIENTS: WATER; GLYCERIN; ALCOHOL

Lymph 1 Acute Homeopathic Liquid

Active Ingredients:

Adrenal 3X, 6X

Apis Mellififica 3X, 6X

Adranea diadema 9X, 12X

ATP 4X,6X, 12X, 24X

Belladonna 6X, 12X

Calcarea carbonica 9X

Conium maculatum 6X

Echinacea angustifolia 1X

Fumaria officinalis 6X, 12X

Galium aparine 9X

Graphites naturalis 6X

Hypothalamus 3X, 6X

Kali iodatum 3X, 6X

Lachesis muta 12X

Mesenchyme 9X

Mercurius iodatus flavus 9X

Myristica sebefera 9X

Phosphorus 12X

Phytolacca decandra 2X, 9X

Pinus maritima 6X

Pituitary 3X, 6X

Rhus toxicodendron 12X

Scrophularia nodosa 9X, 15X

Sulphur 12X

Thyroid 6X

Uncaria tomentosa 3X, 6X

Vespa crabro 12X

PURPOSE

Provides Homeopathic Aid in Support of Drainage

Keep out of reach of children

INDICATIONS AND USAGE

30 drops 2X daily in warm water or as recommended by a health care practitioner

Shake well before use

WARNINGS

If you are pregnant, breastfeeding or taking medications consult a healthcare practitioner before use.
Keep out of reach of children.
Do not use if seal is missing or broken.

DOSAGE AND ADMINISTRATION

30 drops 2X daily or as recommended by a health care practitioner

INACTIVE INGREDIENT

Reversed osmosis water
vegetable glycerin
alcohol (ethanol)

PACKAGE LABEL

bottlelabel.jpg
image of bottle label

LA1